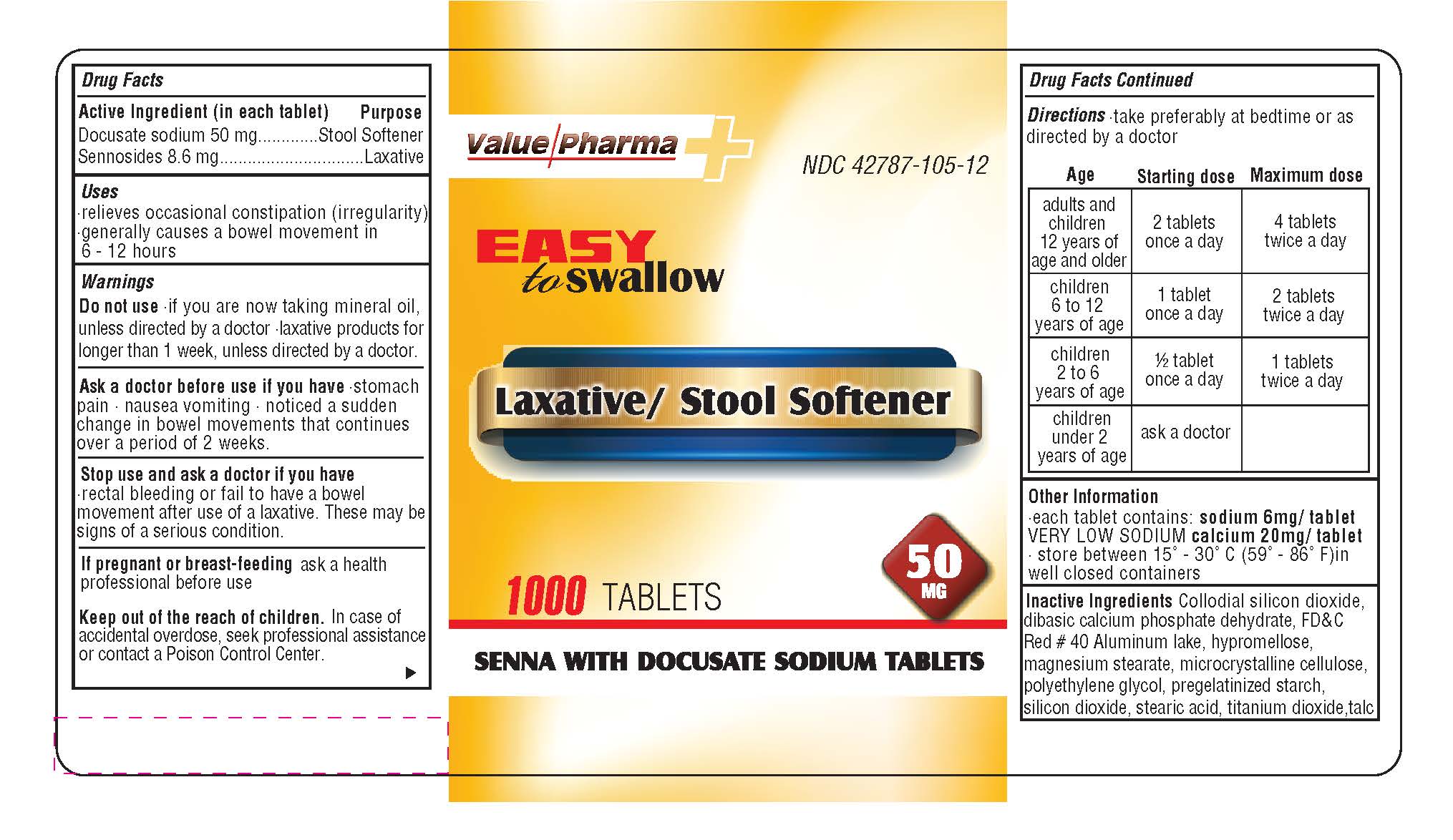 DRUG LABEL: SENOKOT-S
NDC: 42787-105 | Form: PILL
Manufacturer: Ajes Pharmaceuticals,LLC
Category: otc | Type: HUMAN OTC DRUG LABEL
Date: 20140525

ACTIVE INGREDIENTS: DOCUSATE SODIUM 50 mg/340 mg; SENNOSIDES 8.6 mg/340 mg
INACTIVE INGREDIENTS: COLLOIDAL SILICON DIOXIDE; DIBASIC CALCIUM PHOSPHATE DIHYDRATE; FD&C BLUE NO. 2; FD&C RED NO. 40; STEARIC ACID; TITANIUM DIOXIDE; TALC; HYPROMELLOSES; MAGNESIUM STEARATE; CELLULOSE, MICROCRYSTALLINE

Drug Facts

Active Ingredients (in each tablet)

Docusate sodium 50 mg

Sennosides 8.6 mg

Purpose

Stool Softner

Laxative

Keep Out of Reach of Children

In case of overdose, get medical help or contact

a Poison Control Center right away.

Uses

Relieves occasional constipation (irregularity)

Generally causes a bowel movement in 6-12 hours

Warnings

Do Not Use

If you are now taking mineral oil,

unless directed by a doctor

Laxative products for longer than 1 week,

unless directed by a doctor

DOSAGE AND ADMINISTRATION

Directions - take preferably at bedtime or as directed by a doctor

Age Starting dose Maximum Dose

Adults and children 12 years of age or older 2 tablets once a day - 4 tablets twice a day

children 6 to 12 years of age - 1 tablet once a day 2 tablets twice a day

children 2 to 6 years of age 1/2 tablet once a day 1 tablet twice a day

children under 2 years of age ask a doctor

INACTIVE INGREDIENT

Enter section

Ask a doctor before use if your have rectal bleeding or fail to have

a bowel movement after use of a laxative. These may be signs of

a serious condition

PREGNANCY

If pregnant or breast-feeding ask a health professional before use